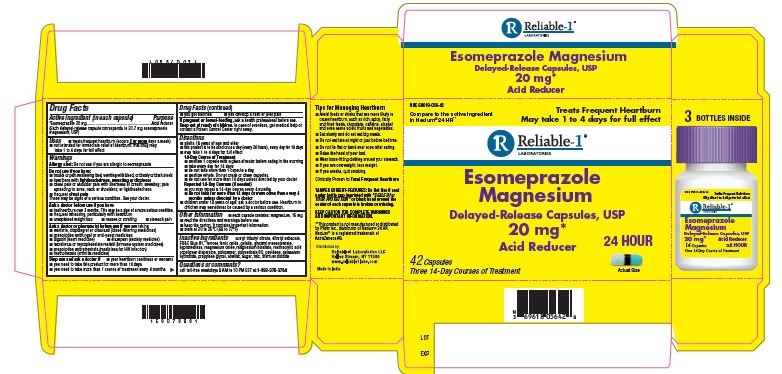 DRUG LABEL: Esomeprazole
NDC: 69618-056 | Form: CAPSULE
Manufacturer: Reliable 1 Laboratories
Category: otc | Type: HUMAN OTC DRUG LABEL
Date: 20210809

ACTIVE INGREDIENTS: ESOMEPRAZOLE MAGNESIUM 20 mg/1 1
INACTIVE INGREDIENTS: GELATIN; GLYCERYL MONOSTEARATE; POLYSORBATE 80; HYPROMELLOSE, UNSPECIFIED; MAGNESIUM STEARATE; POVIDONE; POTASSIUM HYDROXIDE; SHELLAC; FD&C BLUE NO. 1; MAGNESIUM OXIDE; DIBUTYL SEBACATE; FERROSOFERRIC OXIDE; METHACRYLIC ACID - ETHYL ACRYLATE COPOLYMER (1:1) TYPE A; PROPYLENE GLYCOL; POLOXAMER 188; ACETYLTRIBUTYL CITRATE; TITANIUM DIOXIDE; SUCROSE; TALC

Reliable-1 Esomeprazole Magnesium DR Capsules

Active ingredient (in each capsule)

*Esomeprazole 20 mg (Each delayed-release capsule corresponds to 20.7 mg esomeprazole magnesium, USP)

Purpose

Acid reducer

Uses

treats frequent heartburn (occurs 2 or more days a week)

not intended for innediate relief of heartburn: this drug may take 1 to 4 days for full effect

Warnings

Allergy alert: Do not use if you are allergic to esomeprazole

Do not use if you have:

trouble or pain swallowing food, vomiting with blood, or bloody or black stools

heartburn with lightheadedness, sweating or dizziness

chest pain or shoulder pain with shortness of breath; sweating; pain spreading to arms, neck or shoulders; or lightheadedness

frequent chest pain

These may be sings of a serious condition. See your doctor.

Ask a doctor before use if you have

had heartburn over 3 months. This may be a sign of a more serious condition.

frequent wheezing, particulary with heartburn

unexplained weight loss

nausea or vomiting

stomach pain

Ask a doctor or pharmacist before use if you are taking

warfarin, clopifogrel or cilostazol (blood-thinning medicines)

prescription antifungal or anti-yeast medications

digozin (heart medicine)

diazepam (anxiety medicine)

tacrolimus or mycophenolate mofetil (immune system medicines)

prescription antiretovirals (medicines for HIV infections)

methotrexate (arthritis medicine)

Stop use and ask a doctor if

your heartburn continues or worsens

you need to take this prodcut for more than 14 days

you need to take more than 1 course of treatment every 4 months

you get diarrhea

you develop a rash or joint pain

PREGNANCY OR BREAST FEEDING

If pregnant or breast-feeding, ask a health prefessional before use

KEEP OUT OF REACH OF CHILDREN

In case of overdose, get medical help or contract a Posion Control Center right away.

Directions

adults 18 years of age and older

this prodcut is to be used once a day (every 24 hours), every day for 14 days

make take 1 to 4 days for full effect

14-Day Course of Treatment

swallow 1 capsule with a glass of water before eating in the morning

take every day for 14 days

do not take more than 1 capsule a day

swallow whole. Do not crush or chew capsules.

do not use of more than 14 days unless directed by your doctor

Repeated 14-Day Courses (if needed)

you may repeart a 14-day course every 4 months

do not take for more than 14 days or more often than every 4 mounths unless directed by a doctor

children under 18 years of age: ask a doctor before use. Heartburn in children may sometimes be cuased by a serious condition.

Other Information

each capsule contains: magnesium, 15 mg

read the directions and warmings before use

keep the carton. It contains important information.

store at 20-25ºC (68 to 77ºF)

Inactive ingredients

acetyl tributyl citrate, dibutyl sebacate, FD&C Blue #1, ferroso ferric oxide, gelatin, glyceryl monostearate, hypromellose, magnesium odixe, magnesium stearate, methacrylic acid copolymer dispersion, poloxamer, polysorbate 80, povidone, potassium hydroxide, propylene glycol, shellac, sugar, talc, titanium dioxide

Questions or comments?

call tool-free weekdays 8 AM to 10 PM EST at 1-888-375-3784

PACKAGE LABEL

NDC 69618-056-42

Compare to the active ingredient in Nexium® 24 HR**

Esomeprazole Magnesium

Delayed-Release Capsules, USP

20 mg*

Acid Reducer

42 Capsules

Three 14-day Courses of Treatment